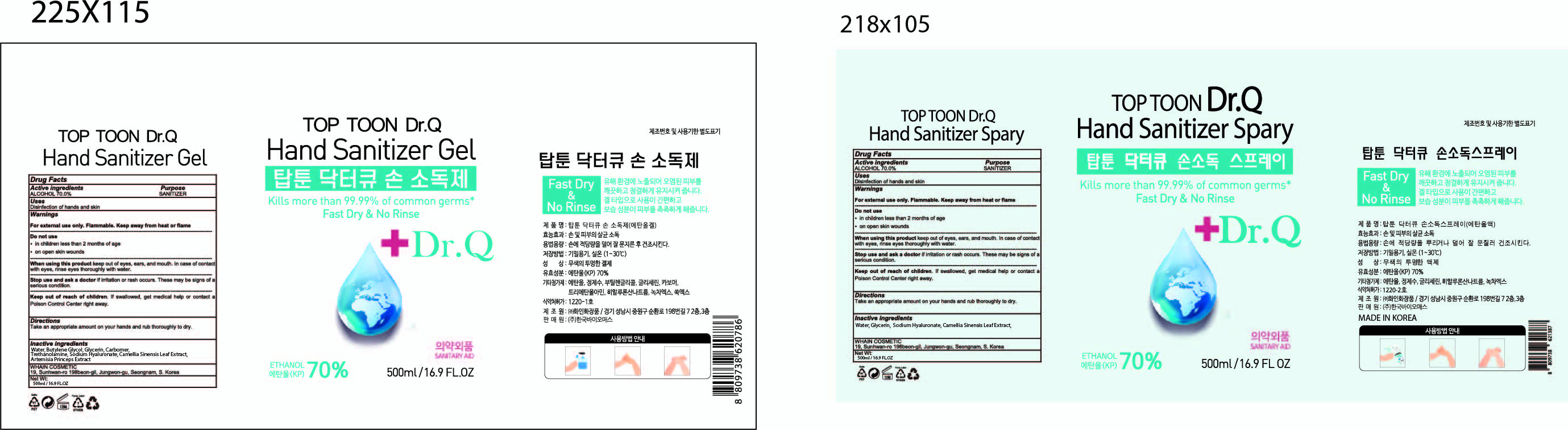 DRUG LABEL: TOP TOON Dr.Q Hand Sanitizer Gel
NDC: 73823-201 | Form: GEL
Manufacturer: WHAIN COSMETIC
Category: otc | Type: HUMAN OTC DRUG LABEL
Date: 20210119

ACTIVE INGREDIENTS: ALCOHOL 350 mL/500 mL
INACTIVE INGREDIENTS: BUTYLENE GLYCOL; WATER; ARTEMISIA PRINCEPS LEAF; GREEN TEA LEAF; CARBOMER HOMOPOLYMER, UNSPECIFIED TYPE; TROLAMINE; GLYCERIN; HYALURONATE SODIUM

[WHAIN COSMETIC] TOP TOON Dr.Q Hand Sanitizer Gel
73823-201-01